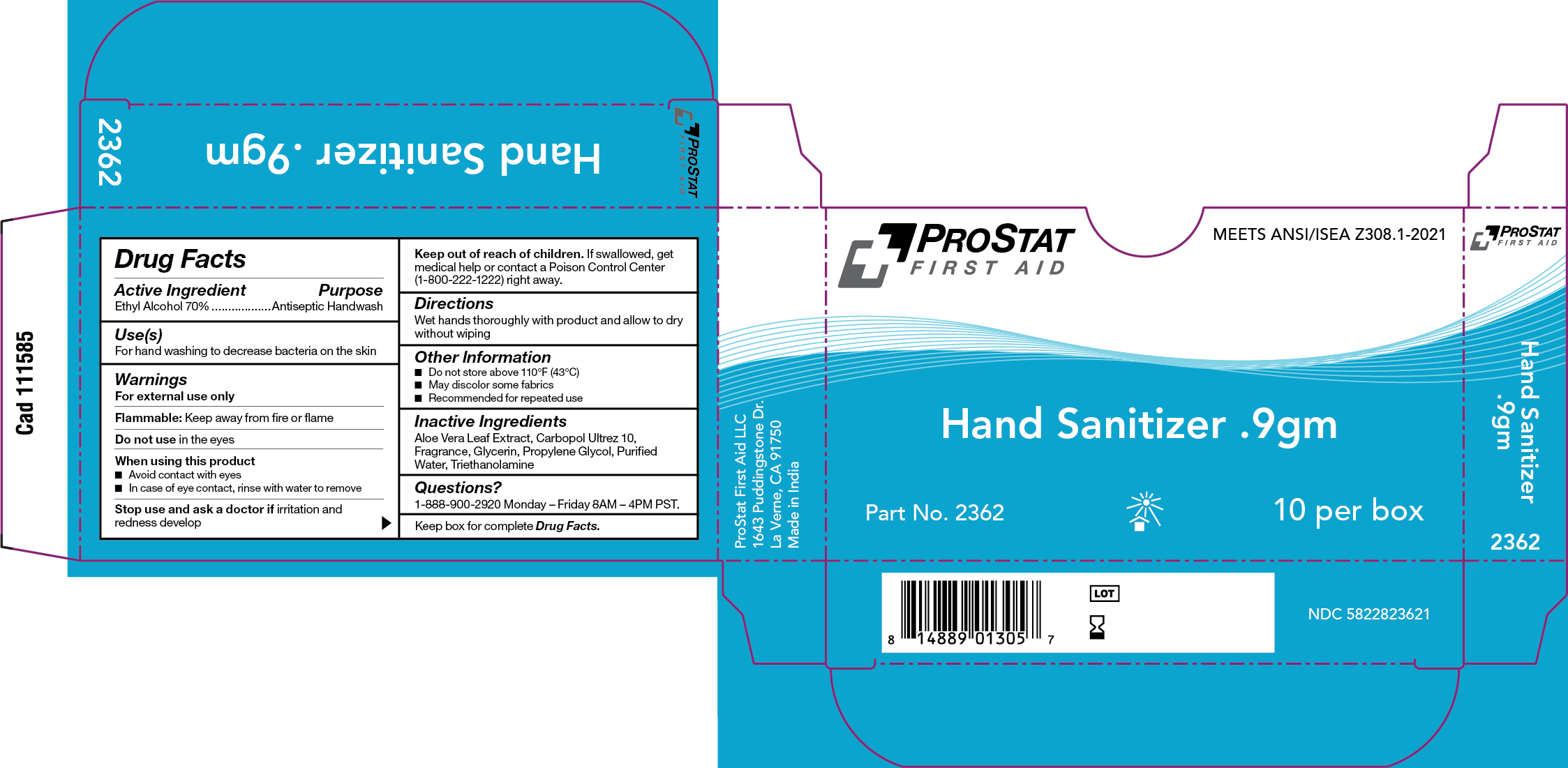 DRUG LABEL: PS-2362 Hand Sanitizer 0.9g packet
NDC: 58228-2362 | Form: GEL
Manufacturer: ProStat First Aid LLC
Category: otc | Type: HUMAN OTC DRUG LABEL
Date: 20251215

ACTIVE INGREDIENTS: ALCOHOL 70 mL/100 mL
INACTIVE INGREDIENTS: CARBOMER INTERPOLYMER TYPE A (ALLYL SUCROSE CROSSLINKED); WATER; GLYCERIN; PROPYLENE GLYCOL; TROLAMINE; ALOE VERA LEAF

PS-2362 Hand Sanitizer 0.9g Packet

Active Ingredient

Ethyl Alcohol 70%

Purpose

Antiseptic Handwash

Use(s)

For hand washing to decrease bacterial on the skin

Warnings

For External Use Only

Flammable

Keep away from fire or flame

Do not use

In the eyes

When using this product

• Avoid contact with eyes

• In case of eye contact, rinse with water to remove

Stop use and ask a doctor if

Irritation and redness develop

Keep out of reach of children

If swallowed, get medical help or contact a Poison Control Center (1-800-222-1222) right away.

Directions

Wet hands thoroughly with product and allow to dry without wiping

Inactive Ingredients

Aloe Vera Leaf Extract, Carbopol Ultrez 10, Fragrance, Glycerin, Propylene Glycol, Purified Water, Triethanomlamine

Questions?

1-888-900-2920 Monday - Friday 8AM - 4PM PST

Label

PS-2362 Hand Sanitizer